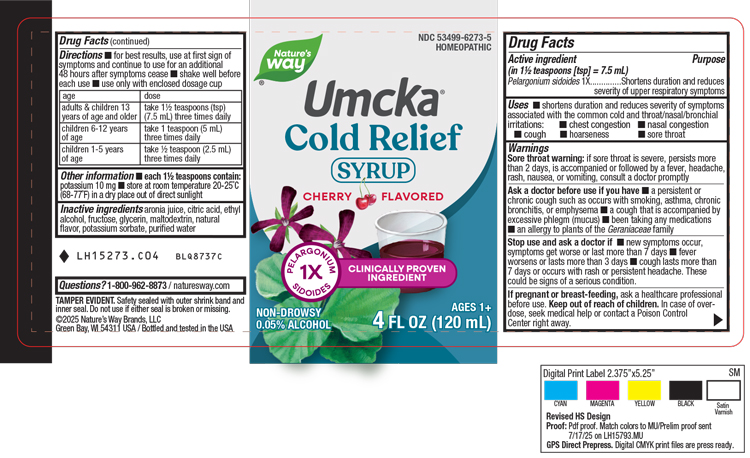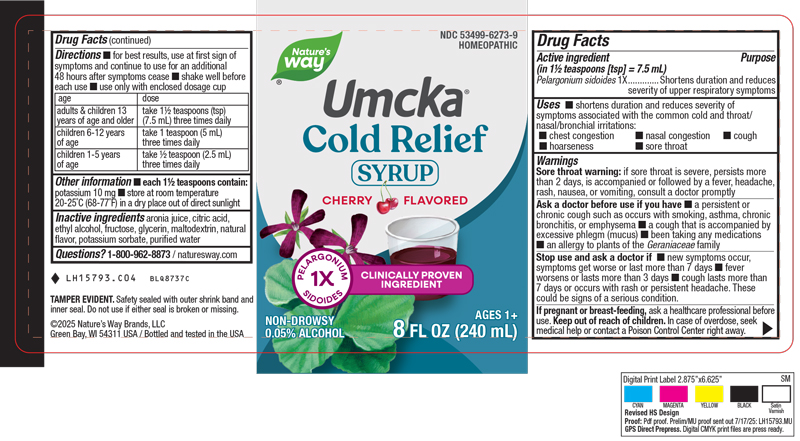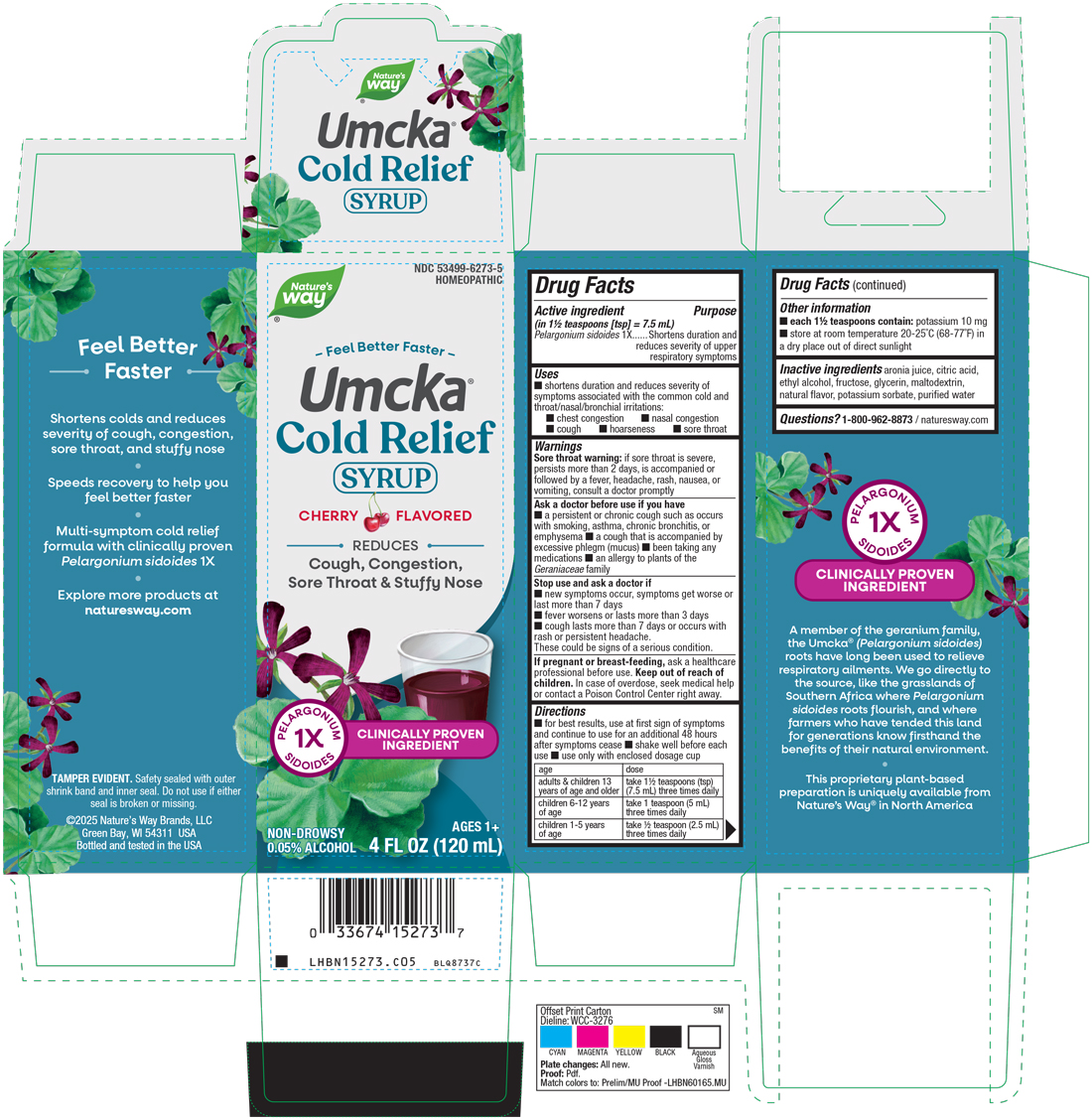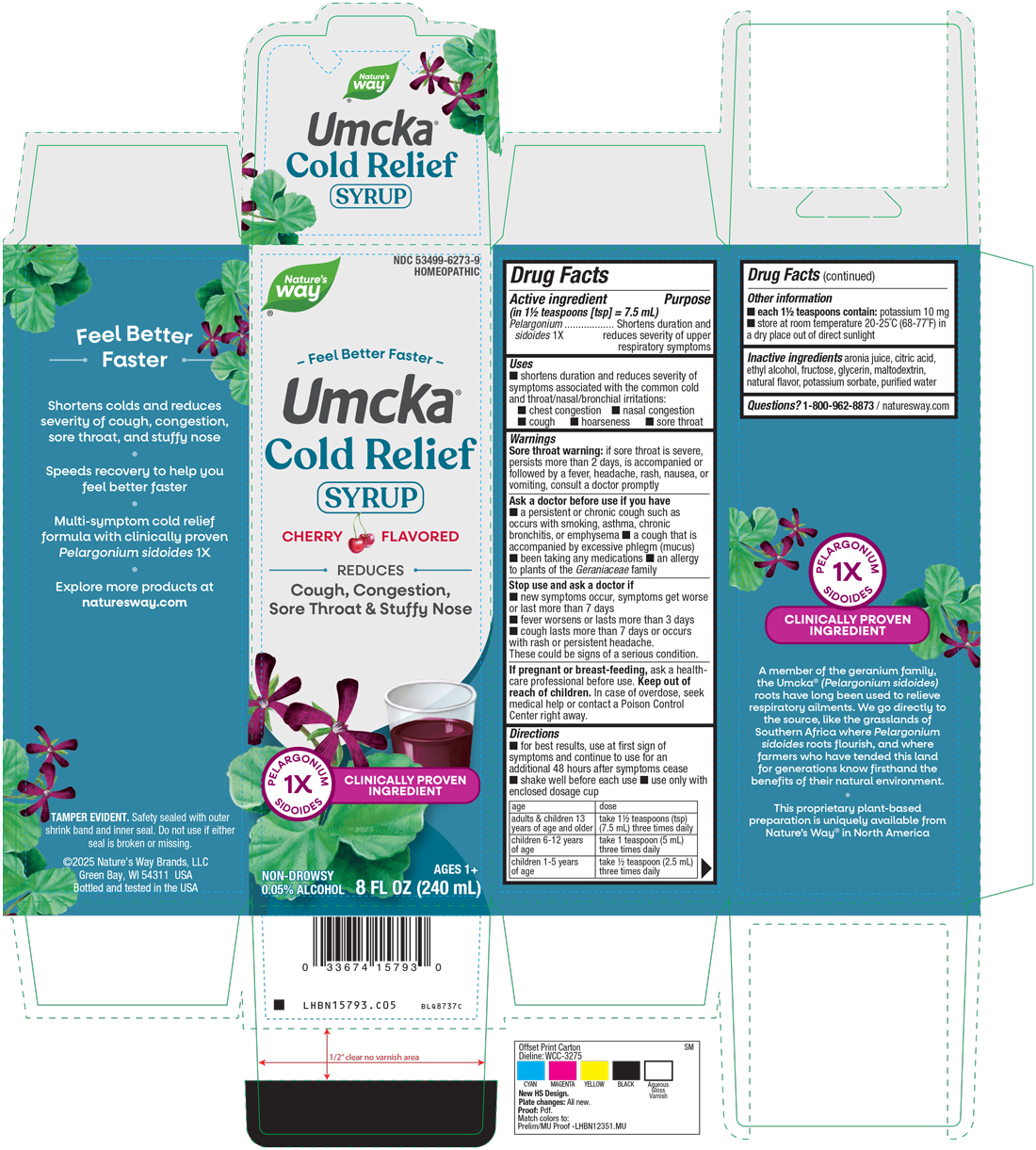 DRUG LABEL: Cold Relief Syrup Cherry
NDC: 53499-6273 | Form: SYRUP
Manufacturer: Schwabe North America, Inc
Category: homeopathic | Type: HUMAN OTC DRUG LABEL
Date: 20250917

ACTIVE INGREDIENTS: PELARGONIUM SIDOIDES ROOT 1 [hp_X]/240 mL
INACTIVE INGREDIENTS: ARONIA MELANOCARPA FRUIT JUICE; ANHYDROUS CITRIC ACID; ALCOHOL; FRUCTOSE; MALTODEXTRIN; WATER; POTASSIUM SORBATE; GLYCERIN

Cold Relief Cherry Syrup

Active Ingredient

Pelargonium sidoides 1X

Inactive Ingredients

Aronia Juice

Citric Acid

Ethyl Alcohol

Fructose

Glycerin

Maltodextrin

Natural Flavor

Potassium Sorbate

Purified Water

Dosage & Administration:

For best results, use at first sign of symptoms and continue to use for an additional 48 hours after symptoms cease.

Shake well before each use.

Use only with enclosed dosage cup.

Adults and children 13 years of age and older: Take 1 ½ teaspoon (tsp) (7.5 mL) three times daily.

Children 6-12 years of age: Take 1 teaspoon (5 mL) three times daily.

Children 1-5 years of age: Take ½ teaspoon (2.5 mL) three times daily.

Indications and Usage Section

Shortens duration and reduces severity of symptoms associated with the common cold and throat/nasal/bronchial irritations: chest congestion, nasal congestion, cough, hoarseness, sore throat.

Purpose

Shortens duration and reduces severity of symptoms associated with the common cold and throat/nasal/bronchial irritations: chest congestion, nasal congestion, cough, hoarseness, sore throat.

Warnings

Sore throat warning: if sore throat is severe, persists more than 2 days, is accompanied or followed by a fever, headache, rash, nausea, or vomiting, consult a doctor promptly.

Ask Doctor

Ask a doctor before use if you have a persistent or chronic cough such as occurs with smoking, asthma, chronic bronchitis, or emphysema, a cough that is accompanied by excessive phlegm (mucus), been taking any medications, an allergy to plants of the Geraniaceae family.

Stop Use

Stop use and ask a doctor if new symptoms occur, symptoms get worse or last more than 7 days, fever worsens or lasts more than 3 days, cough lasts more than 7 days or occurs with rash or persistent headache.

These could be signs of a serious condition.

Pregnancy or Breast Feeding

If pregnant or breast-feeding, ask a healthcare professional before use.

Keep out of reach of children

Overdose

In case of overdose, seek medical help or contact a Poison Control Center right away.